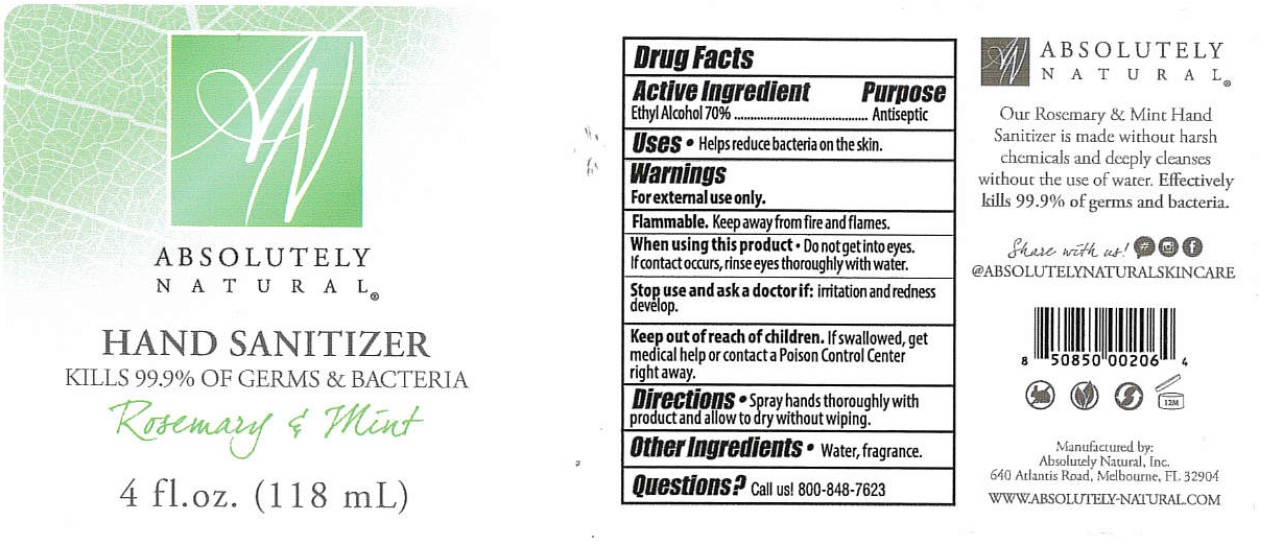 DRUG LABEL: Absolutely Natural Rosemary and Mint Hand Sanitizer
NDC: 70793-011 | Form: SPRAY
Manufacturer: Absolutely Natural, Inc.
Category: otc | Type: HUMAN OTC DRUG LABEL
Date: 20241211

ACTIVE INGREDIENTS: ALCOHOL 70 mL/100 mL
INACTIVE INGREDIENTS: WATER

ABSOLUTELY NATURAL® HAND SANITIZER Rosemary & Mint

Active Ingredient

Ethyl Alcohol 70%

Purpose

Antiseptic

Uses

• Helps reduce bacteria on the skin.

Warnings

For external use only.

Flammable. Keep away from fire and flames.

When using this product • Do not get into eyes. If contact occurs, rinse eyes thoroughly with water.

Stop use and ask a doctor if: irritation and redness develop.

Keep out of reach of children. If swallowed, get medical help or contact a Poison Control Center right away.

Directions

• Spray hands thoroughly with product and allow to dry without wiping.

Other Ingredients

• Water, fragrance.

Questions?

Call us! 800-848-7623

KILLS 99.9% OF GERMS & BACTERIA

Our Rosemary & Mint Hand Sanitizer is made without harsh chemicals and deeply cleanses without the use of water. Effectively kills 99.9% of germs and bacteria.

Share with us!

@ABSOLUTELYNATURALSKINCARE

Manufactured by:

Absolutely Natural, Inc.

640 Atlantis Road, Melbourne, FL, 32904

WWW.ABSOLUTELY-NATURAL.COM